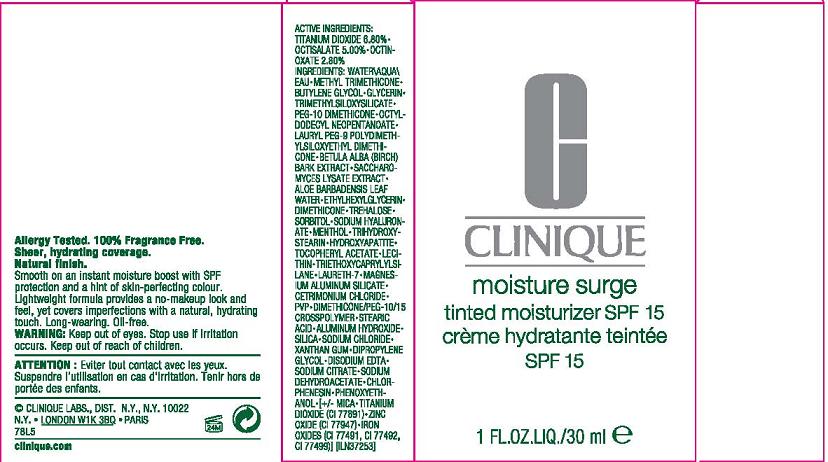 DRUG LABEL: MOISTURE SURGE
NDC: 49527-007 | Form: LOTION
Manufacturer: CLINIQUE LABORATORIES INC
Category: otc | Type: HUMAN OTC DRUG LABEL
Date: 20110114

ACTIVE INGREDIENTS: TITANIUM DIOXIDE 6.8 mL/100 mL; OCTISALATE 5.0 mL/100 mL; OCTINOXATE 2.8 mL/100 mL
INACTIVE INGREDIENTS: BUTYLENE GLYCOL; WATER; DIMETHICONE

ACTIVE INGREDIENT

active ingredients: titanium dioxide 6.80% [] octisalate 5.00% [] octinoxate 2.80%

INACTIVE INGREDIENT

inactive ingredients: water\aqua\eau [] methyl trimethicone [] butylene glycol [] glycerin [] trimethylsiloxysilicate [] peg-10 dimethicone [] octyldodecyl neopentanoate [] lauryl peg-9 polydimethylsiloxyethyl dimethicone [] betula alba (birch) bark extract [] saccharomyces lysate extract [] aloe barbadensis leaf water [] ethylhexylglycerin [] dimethicone [] trehalose [] sorbitol [] sodium hyaluronate [] menthol [] trihydroxystearin [] hydroxyapatite [] tocopheryl acetate [] lecithin [] triethoxycaprylylsilane [] laureth-7 [] magnesium aluminum silicate [] cetrimonium chloride [] pvp [] dimethicone/peg-10/15 crosspolymer [] stearic acid [] aluminum hydroxide [] silica [] sodium chloride [] xanthan gum [] dipropylene glycol [] disodium edta [] sodium citrate [] sodium dehydroacetate [] chlorphenesin [] phenoxyethanol [] [+/- mica [] titanium dioxide (ci 77891) [] zinc oxide (ci 77947) [] iron oxides (ci 77491, ci 77492, ci 77499)

WARNINGS

warning: Keep out of eyes. stop use if irritation occurs.

keep out of reach of children

PACKAGE LABEL

principal display panel:
CLINIQUE
MOISTURE SURGE
TINTED MOISTURIZER
SPF 15
1 FL OZ LIQ/ 30 ML
CLINIQUE LABS DIST
NY NY 10022